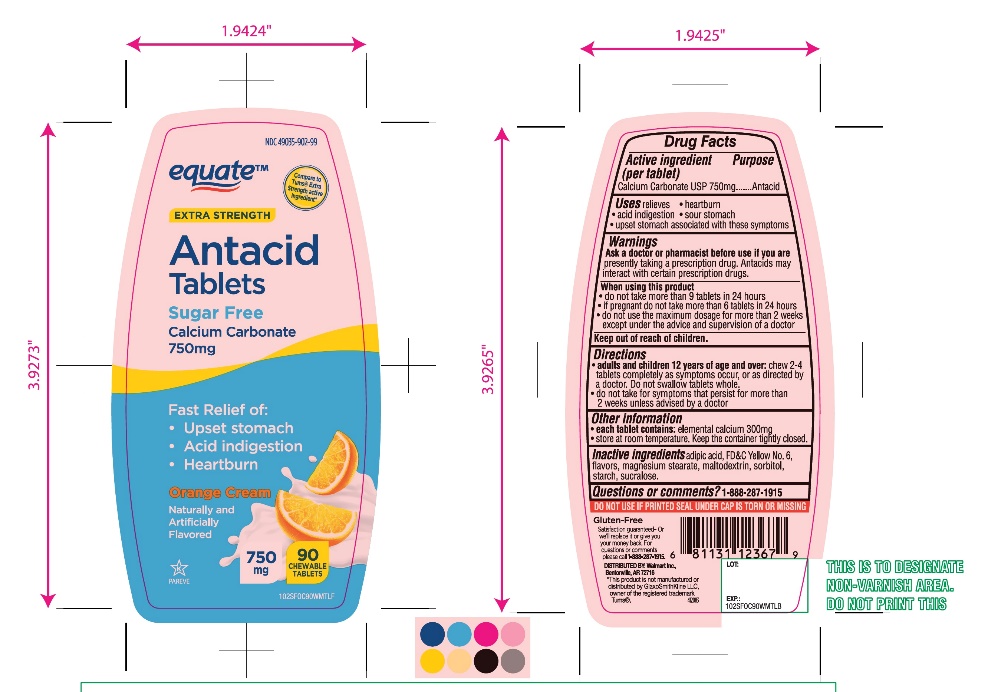 DRUG LABEL: equate Sugar Free Extra Strength Antacid

NDC: 49035-902 | Form: TABLET, CHEWABLE
Manufacturer: Wal-Mart Stores,Inc.,
Category: otc | Type: HUMAN OTC DRUG LABEL
Date: 20251027

ACTIVE INGREDIENTS: CALCIUM CARBONATE 750 mg/1 1
INACTIVE INGREDIENTS: ADIPIC ACID; FD&C YELLOW NO. 6; MAGNESIUM STEARATE; MALTODEXTRIN; SORBITOL; STARCH, CORN; SUCRALOSE

Equate Sugar Free Extra Strength Antacid Calcium Carbonate

Active ingredient (per tablet)

Calcium Carbonate USP 750 mg

Purpose

Antacid

Uses

relieves

• heartburn

• acid indigestion

• sour stomach

• upset stomach associated with these symptoms

Warnings

Ask a doctor or pharmacist before use if you arepresently taking a prescription drug. Antacids may interact with certain prescription drugs.

When using this product

- do not take more than 9 tablets in 24 hours
- If pregnant do not take more than 6 tablets in 24 hours
- do not use the maximum dosage for more than 2 weeks except under the advice and supervision of a doctor

Directions

- adults and children 12 years of age and over:chew 2-4 tablets as symptoms occur ,or as directed by a doctor. Do not swallow tablets whole.
- do not take for symptoms that persist for more than 2 weeks unless advised by a doctor

Other Information

• each tablet contains: elemental calcium 300 mg

• store at room temperature. Keep the container tightly closed.

Inactive ingredients

adipic acid, flavors, magnesium stearate, maltodextrin, sorbitol, starch, sucralose, yellow 6 lake.

Questions?

1-888-287-1915

Safety sealed: Do not use if printed seal under cap is torn or missing

Package/Label Principal Display Panel

NDC 49035-902-99

equate™

Compare to Tums® Sugar Free Extra Strength Active Ingredient*

SUGAR FREE

Extra Strength

Antacid

Calcium Carbonate

Starts Working in Seconds to Relieve:

- Heartburn
- Acid indigestion
- Sour stomach
- Orange Cream Flavor

750 mg

90 CHEWABLE TABLETS

GLUTEN-FREE

Satisfaction guaranteed-

For questions or comments, please call

1-888-287-1915.

DISTRIBUTED BY: Wal-Mart Stores, Inc.,

Bentonville,AR 72716

*This product is not manufactured or distributed by GlaxoSmithKline LLC, owner of the registered trademark, Tums®.